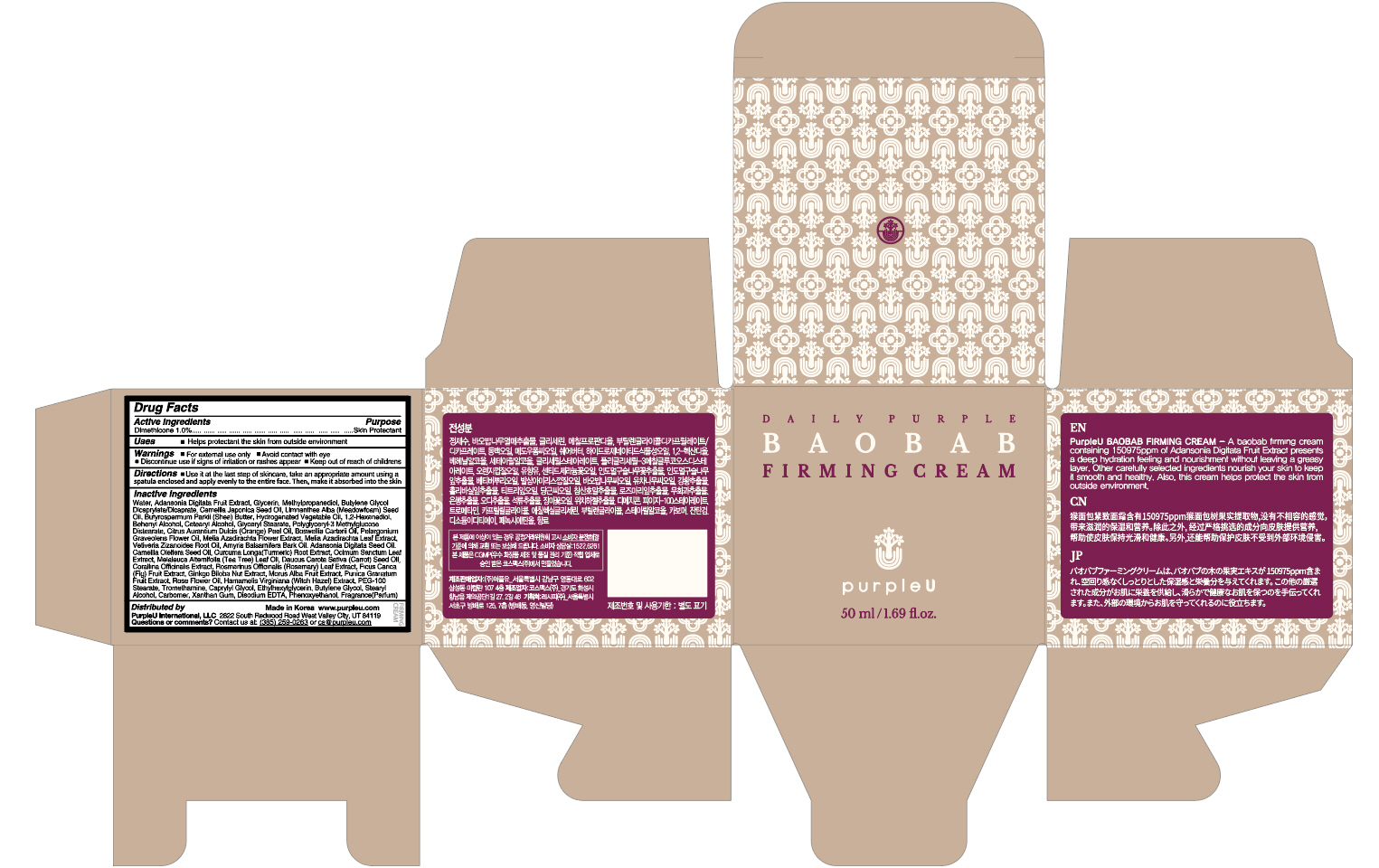 DRUG LABEL: PurpleU BAOBAB FIRMING
NDC: 71732-010 | Form: CREAM
Manufacturer: Recipe Co., Ltd.
Category: otc | Type: HUMAN OTC DRUG LABEL
Date: 20200819

ACTIVE INGREDIENTS: Dimethicone 0.5 g/50 mL
INACTIVE INGREDIENTS: Water; ADANSONIA DIGITATA FRUIT; Glycerin

ACTIVE INGREDIENT

Dimethicone 1.0%

INACTIVE INGREDIENTS

Water, Adansonia Digitata Fruit Extract, Glycerin, Methylpropanediol, Butylene Glycol Dicaprylate/Dicaprate, Camellia Japonica Seed Oil, Limnanthes Alba (Meadowfoam) Seed Oil, Butyrospermum Parkii (Shea) Butter, Hydrogenated Vegetable Oil, 1,2-Hexanediol, Behenyl Alcohol, Cetearyl Alcohol, Glyceryl Stearate, Polyglyceryl-3 Methylglucose Distearate, Citrus Aurantium Dulcis (Orange) Peel Oil, Boswellia Carterii Oil, Pelargonium Graveolens Flower Oil, Melia Azadirachta Flower Extract, Melia Azadirachta Leaf Extract, Vetiveria Zizanoides Root Oil, Amyris Balsamifera Bark Oil, Adansonia Digitata Seed Oil, Camellia Oleifera Seed Oil, Curcuma Longa (Turmeric) Root Extract, Ocimum Sanctum Leaf Extract, Melaleuca Alternifolia (Tea Tree) Leaf Oil, Daucus Carota Sativa (Carrot) Seed Oil, Corallina Officinalis Extract, Rosmarinus Officinalis (Rosemary) Leaf Extract, Ficus Carica (Fig) Fruit Extract, Ginkgo Biloba Nut Extract, Morus Alba Fruit Extract, Punica Granatum Fruit Extract, Rose Flower Oil, Hamamelis Virginiana (Witch Hazel) Extract, Dimethicone, PEG-100 Stearate, Tromethamine, Caprylyl Glycol, Ethylhexylglycerin, Butylene Glycol, Stearyl Alcohol, Carbomer, Xanthan Gum, Disodium EDTA, Phenoxyethanol, Fragrance(Parfum)

PURPOSE

Skin Protectant

WARNINGS

For external use only
Avoid contact with eyes.
Discontinue use if signs of irritation or rashes appear.
Replace the cap after use.

KEEP OUT OF REACH OF CHILDREN

Uses

■ At the last step of skincare, take an appropriate amount using a spatula enclosed and apply evenly to the entire face. Then, make it absorbed into the skin.

Directions

■ A baobab firming cream containing 150975ppm of Adansonia Digitata Fruit Extract presents a deep hydration feeling and nourishment without leaving a greasy layer. Other carefully selected ingredients nourish your skin to keep it smooth and healthy. Also, this cream helps protect the skin from outside environment.